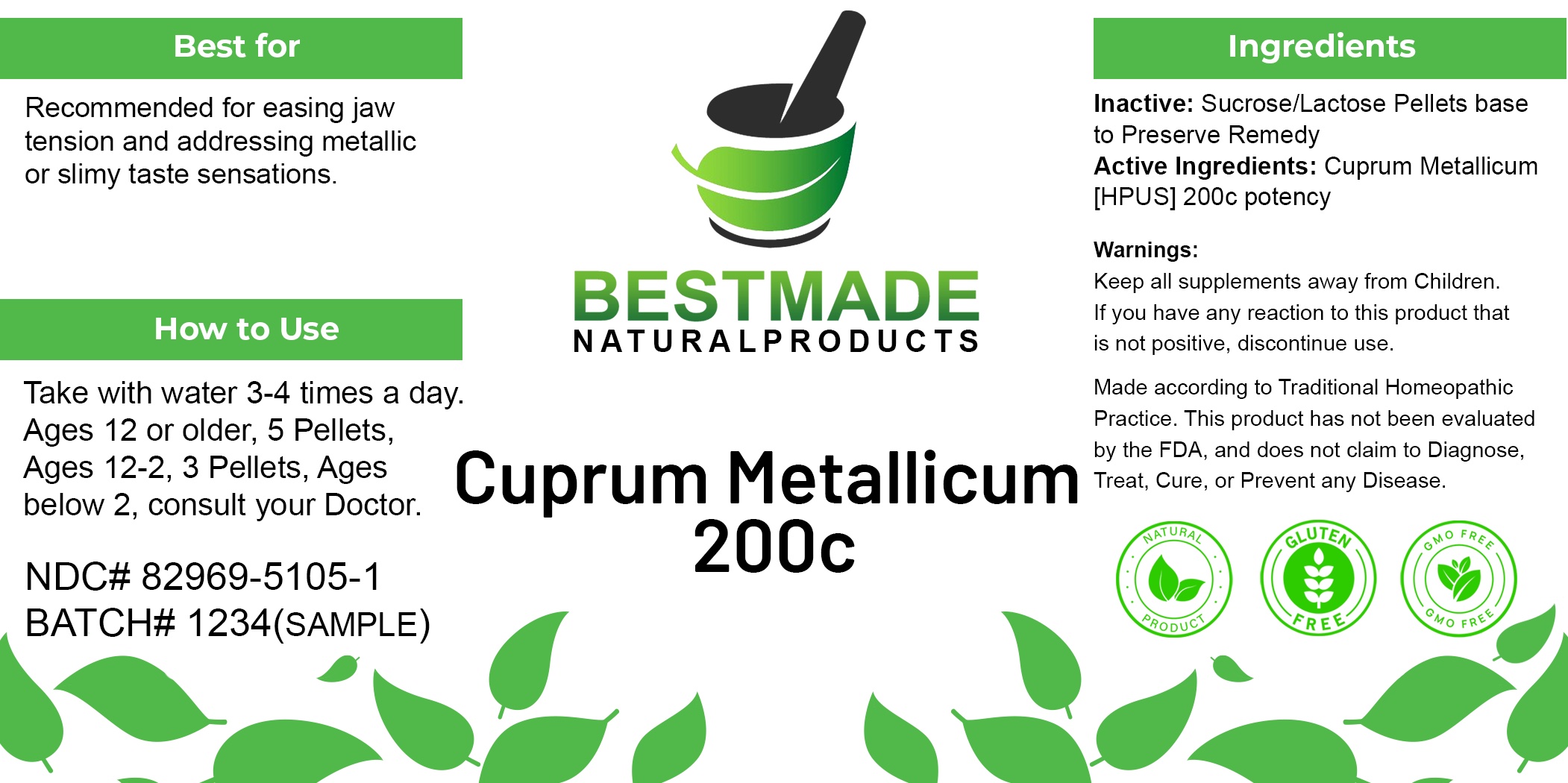 DRUG LABEL: Bestmade Natural Products Cuprum Metallicum
NDC: 82969-5105 | Form: TABLET, SOLUBLE
Manufacturer: Bestmade Natural Products
Category: homeopathic | Type: HUMAN OTC DRUG LABEL
Date: 20241219

ACTIVE INGREDIENTS: COPPER 200 [hp_C]/200 [hp_C]
INACTIVE INGREDIENTS: SUCROSE 200 [hp_C]/200 [hp_C]; LACTOSE 200 [hp_C]/200 [hp_C]

CUPRUM METALLICUM 200C

DOSAGE AND ADMINISTRATION

How to Use
Take with water 3-4 times a day.

Ages 12 or older: 5 pellets
Ages 12-2: 3 pellets
Ages below 2: consult your doctor.

INDICATIONS AND USAGE

Best for
Recommended for easing jaw tension and addressing metallic or slimy taste sensations.

PURPOSE

Best for
Recommended for easing jaw tension and addressing metallic or slimy taste sensations.

INACTIVE INGREDIENT

Ingredients
Inactive: Sucrose/Lactose Pellets base to Preserve Remedy

ACTIVE INGREDIENT

Ingredients
Active Ingredients: Cuprum Metallicum [HPUS] 200c potency

Warnings:

Keep all supplements away from children.

Warnings:

Keep all supplements away from children.
If you have any reaction to this product that is not positive, discontinue use.
Made according to Traditional Homeopathic Practice. This product has not been evaluated by the FDA, and does not claim to diagnose, treat, cure, or prevent any disease.

Entire Package Label